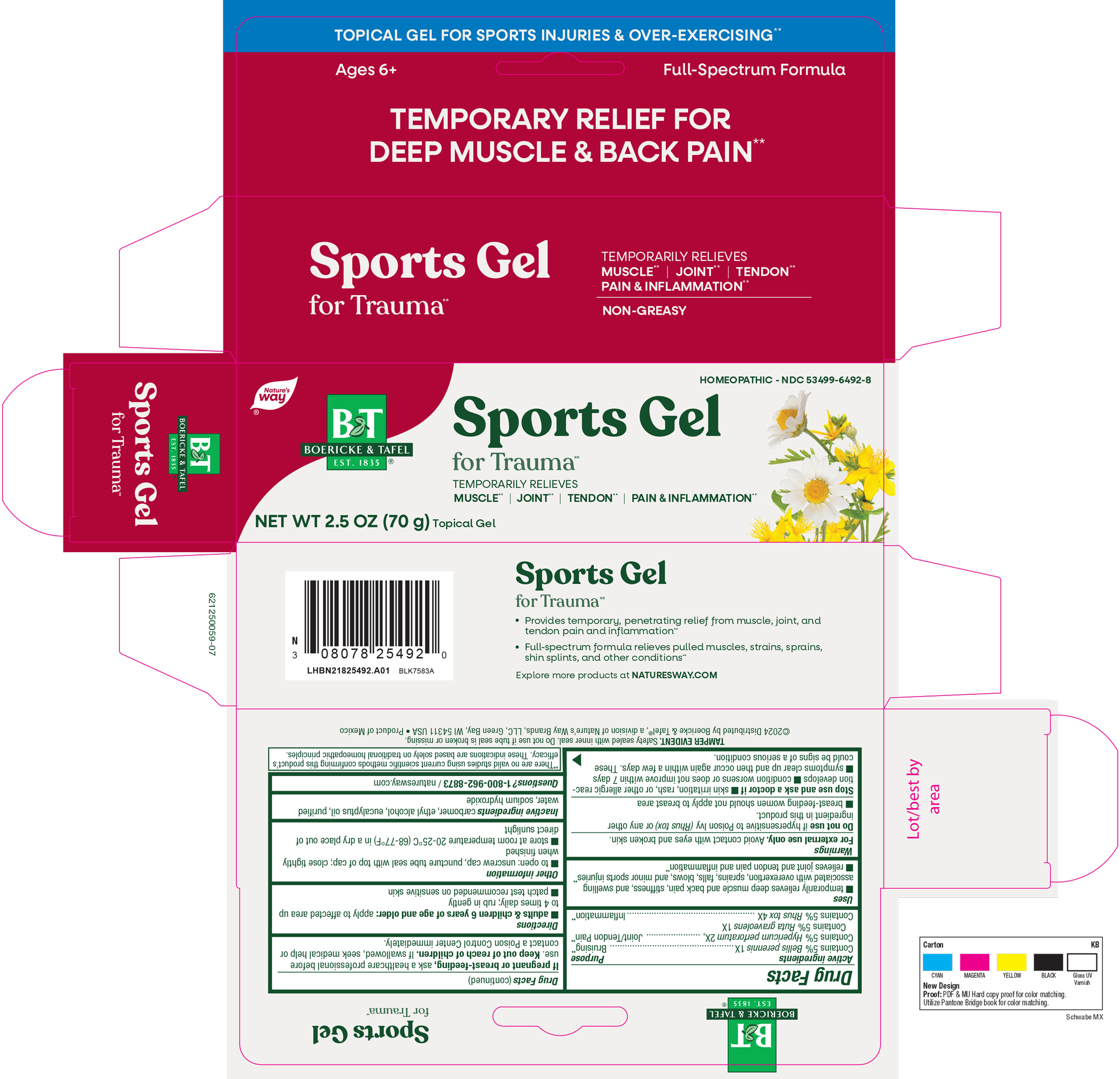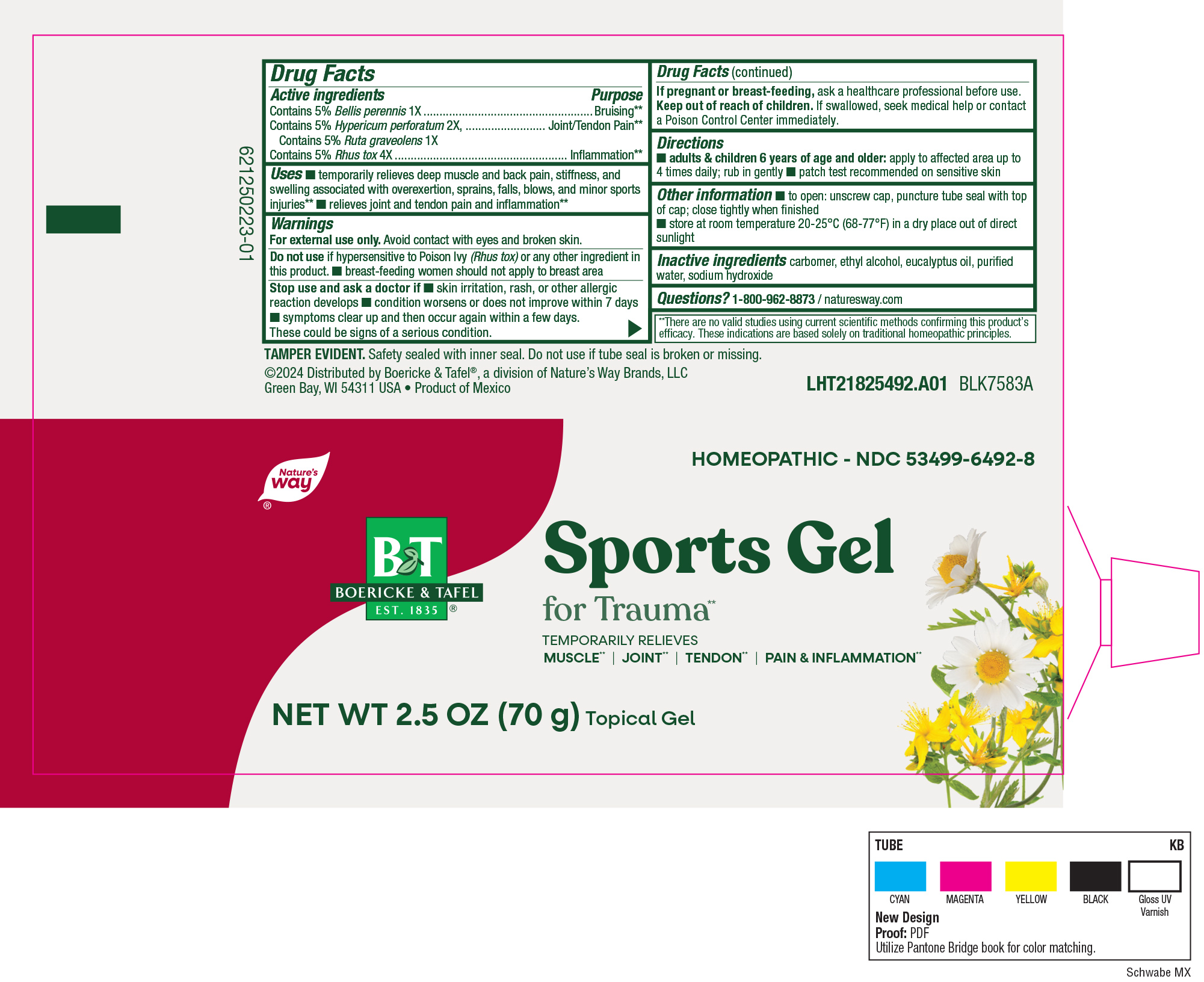 DRUG LABEL: Sports For Trauma Gel
NDC: 68466-1002 | Form: GEL
Manufacturer: Schwabe Mexico, S.A. de C.V.
Category: homeopathic | Type: HUMAN OTC DRUG LABEL
Date: 20251120

ACTIVE INGREDIENTS: BELLIS PERENNIS 1 [hp_X]/70 g; HYPERICUM PERFORATUM 2 [hp_X]/70 g; TOXICODENDRON PUBESCENS LEAF 4 [hp_X]/70 g; RUTA GRAVEOLENS FLOWERING TOP 1 [hp_X]/70 g
INACTIVE INGREDIENTS: ALCOHOL; EUCALYPTUS OIL; CARBOMER HOMOPOLYMER TYPE C; WATER; SODIUM HYDROXIDE

SPORTS GEL FOR TRAUMA

Active Ingredients

Contains 5% Bellis perennis 1X

Contains 5% Hypericum perforatum 2X

Contains 5% Ruta graveolens 1X

Contains 5% Rhus Tox 4X

Inactive Ingredients

Carbomer

Ethyl Alcohol

Eucalyptus Oil

Purified Water

Sodium Hydroxide

Dosage & Administration

Directions

Adults & children 6 years of age and older: apply to affected area up to 4 times daily. Rub in gently.

Patch test recommended on sensitive skin

Indications & Usage

Temporarily relieves deep muscle and back pain, stiffness, and swelling associated with overexertion, sprains, falls, blows, and minor sports injuries.

Relieves joint and tendon pain and inflammation.

Purpose

Temporarily relieves deep muscle and back pain, stiffness, and swelling associated with overexertion, sprains, falls, blows, and minor sports injuries.

Relieves joint and tendon pain and inflammation.

Warnings

For external use only. Avoid contact with eyes and broken skin.

Do not use if hypersensitive to Poison Ivy (Rhus tox) or any other ingredient in this product.

Breast-feeding women should not apply to breast area.

Stop Use

Stop use and ask a doctor if skin irritation, rash, or other allergic reaction develops, condition worsens or does not improve within 7 days, symptoms clear up and then occur again within a few days.

These could be signs of a serious condition.

Pregnancy or Breast feeding

If pregnant or breast-feeding, ask a healthcare professional before use.

Keep out of reach of children

Overdose

If swallowed, seek medical help or contact a Poison Control Center immediately.